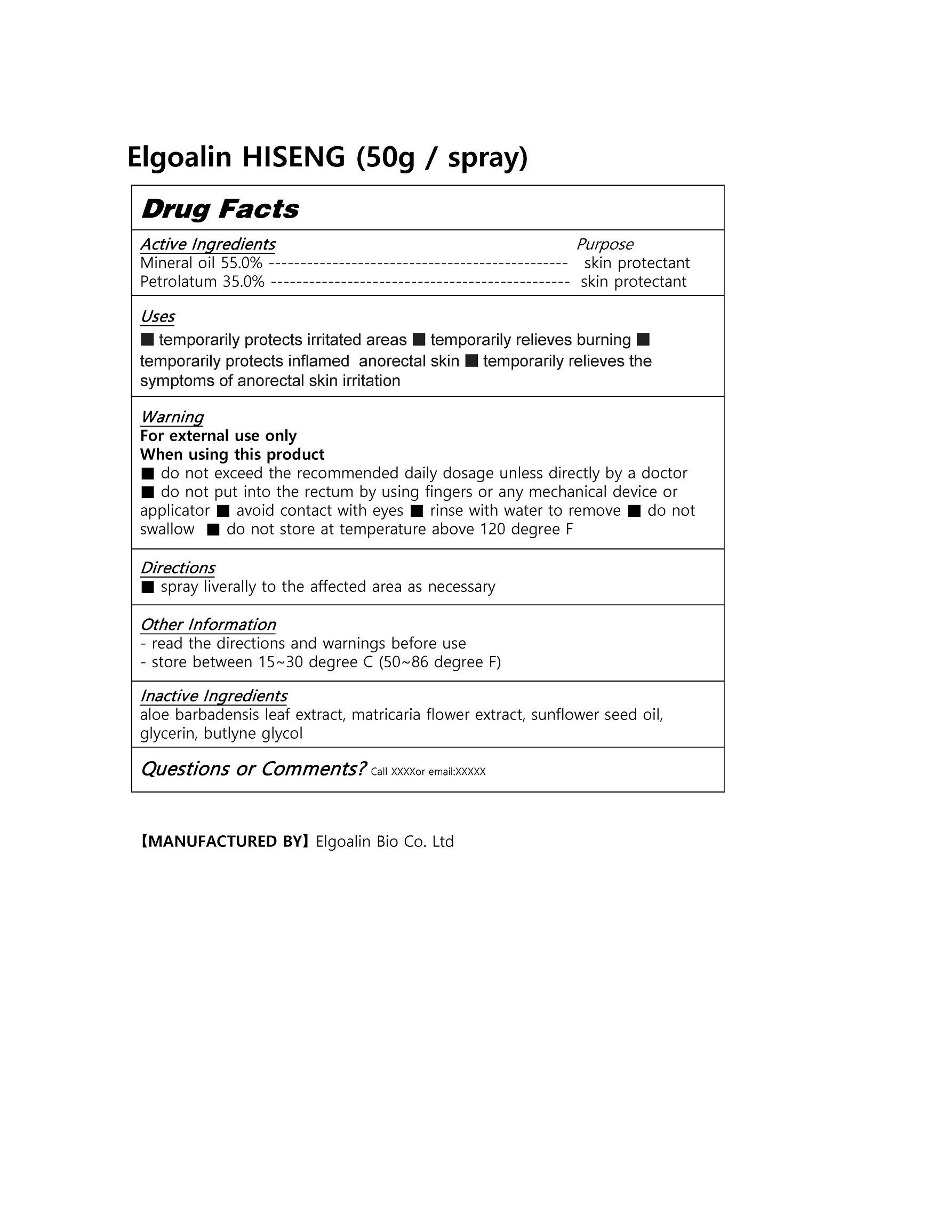 DRUG LABEL: Elgoalin HISENG
NDC: 82677-0001 | Form: LIQUID
Manufacturer: Elgoalin Bio Co.,Ltd
Category: otc | Type: HUMAN OTC DRUG LABEL
Date: 20220417

ACTIVE INGREDIENTS: PETROLATUM 35 g/100 g; MINERAL OIL 55 g/100 g
INACTIVE INGREDIENTS: ALOE VERA LEAF

ACTIVE INGREDIENT

mineral oil, petrolatum

INACTIVE INGREDIENT

aloe barbadensis leaf extract, matricaria flower extract, sunflower seed oil, glycerin, butlyne glycol

PURPOSE

■ temporarily protects irritated areas ■ temporarily relieves burning ■ temporarily protects inflamed anorectal skin ■ temporarily relieves the symptoms of anorectal skin irritation

keep out of reach of the children

INDICATIONS AND USAGE

■ spray liverally to the affected area as necessary

WARNINGS

For external use only

When using this product

■ do not exceed the recommended daily dosage unless directly by a doctor

■ do not put into the rectum by using fingers or any mechanical device or applicator ■ avoid contact with eyes ■ rinse with water to remove ■ do not swallow ■ do not store at temperature above 120 degree F

DOSAGE AND ADMINISTRATION

for external use only